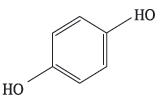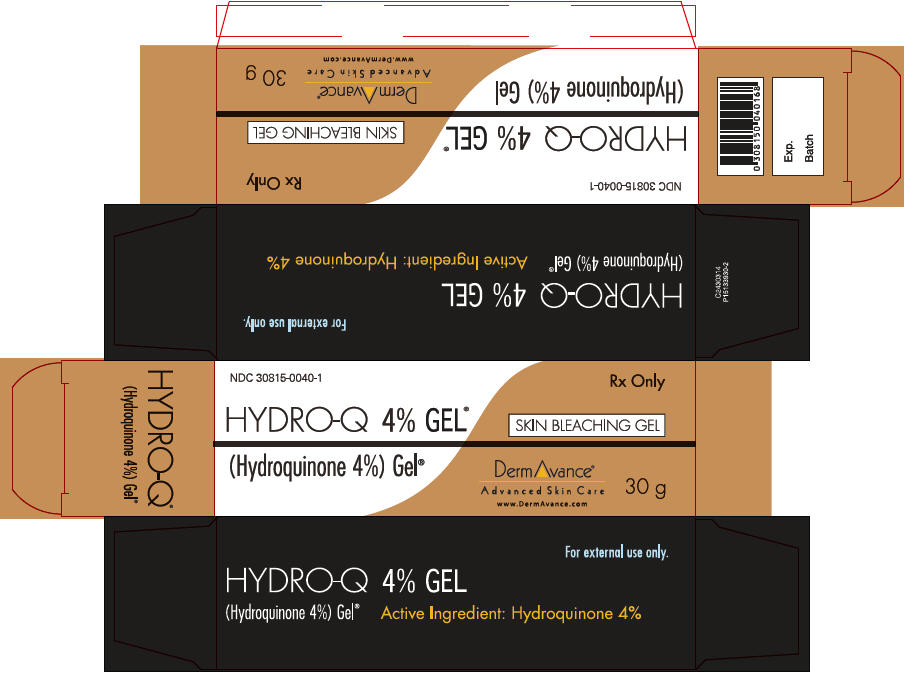 DRUG LABEL: Hydro-Q
NDC: 30815-0040 | Form: GEL
Manufacturer: Dermavance Pharmaceuticals
Category: prescription | Type: HUMAN PRESCRIPTION DRUG LABEL
Date: 20230112

ACTIVE INGREDIENTS: Hydroquinone 40 mg/1 g
INACTIVE INGREDIENTS: Water; CARBOMER HOMOPOLYMER TYPE C (ALLYL PENTAERYTHRITOL CROSSLINKED); SODIUM METABISULFITE; SODIUM HYDROXIDE; METHYLPARABEN; EDETATE DISODIUM

HYDRO-Q® (Hydroquinone 4%) Gel

RX Only

FOR EXTERNAL USE ONLY

DESCRIPTION

HYDRO-Q® contains hydroquinone USP 4%. Hydroquinone is 1, 4-Benzenediol {CAS 123-31-91}. Hydroquinone is structurally related to monobenzone. Hydroquinone occurs as fine white needles. The drug is freely soluble in water and in alcohol and has a pKa of 9.96. Chemically, hydroquinone is designated as p-dihydroxybenzene; the empirical formula is C6H6O2; The molecular weight is 110.1. The structural formula is:

ACTIVE INGREDIENT

Hydroquinone USP 4%

OTHER INGREDIENTS: Purified water, Carbomer 940, Sodium Metabisulfite, Sodium Hydroxide, Methylparaben, Edetate Disodium.

CLINICAL PHARMACOLOGY

Topical application of hydroquinone produces a reversible depigmentation of the skin by inhibition of the enzymatic hydroquinone. oxidation of tyrosine to 3, 4-dihydroxyphenylalanine (dopa) 1 and suppression of other melanocyte metabolic processes. Exposure to sunlight or ultraviolet light will cause regimentation of the bleached areas.

INDICATIONS AND USAGE

HYDRO-Q® is indicated for the gradual bleaching of hyperpigmented skin conditions such as chlosma, melasma, freckles, senile lentigines and areas of melanin hyperpigmentation.

CONTRAINDICATIONS

HYDRO-Q® is contraindicated in any patient that has a prior history of sensitivity or allergic reaction to hydroquinone or any of the other ingredients. The safety of topical hydroquinone use during pregnancy or in children (12 years and under) has not been established.

WARNINGS

1. CAUTION: Hydroquinone is a depigmenting agent that may produce unwanted cosmetic effects if not used as directed. The physician should be familiar with the contents of this insert before prescribing or dispensing this medication.
2. Test for skin sensitivity before using HYDRO-Q® by applying a small amount of the gel to an unbroken patch of skin and check within 24 hours. Minor redness is not a contraindication but where there is itching and vesicle formation or excessive inflammatory response further treatment is not advised. Close patient supervision is recommended. Contact with the eyes should be avoided. If no lightening effect is noted after 2 months of treatment the use of HYDRO-Q® should be discontinued. HYDRO-Q® is formulated for the treatment of dyschromia and should not be used for the prevention of sunburn.
3. Sunscreen use is an essential aspect of hydroquinone therapy because even minimal sunlight sustains melanocytic activity. To prevent repigmentation during treatment and maintenance therapy, sun exposure on treated skin should be avoided by application of a broad spectrum sunscreen SPF 15 or greater) or by use of protective clothing
4. Keep this and all medications out of reach of children. In case of accidental ingestion, contact a physician or a poison control center immediately.
5. WARNING: Contains sodium metabisulfite, a sulfite that may cause serious allergic reactions (e.g., hives, itching, wheezing, anaphylaxis, severe asthma attack) in certain susceptible persons
6. On rare occasions, a gradual blue-black darkening of the skin may occur, in which case, use of HYDRO-Q® should be discontinued and a physician contacted immediately

PRECAUTIONS

See Warnings

A. Pregnancy Category C

Animal reproduction studies have not been conducted with topical hydroquinone. It is also not known whether hydroquinone can cause fetal harm when used topically on a pregnant woman, or can affect reproductive capacity.

B. Nursing mothers

It is not known whether topical hydroquinone is absorbed or excreted in human milk. Caution is advised when used by a nursing mother.

C. Pediatric usage

Safety and effectiveness in pediatric patients below the age of 12 years have not been established.

ADVERSE REACTIONS

No systemic reactions have been reported. Occasional cutaneous hypersensitivity (localized contact dermatitis) may occur, in which case the medication should be discontinued and the physician notified immediately

OVERDOSAGE

There have been no systemic reactions reported from the use of topical hydroquinone. However, treatment should be limited to relatively small areas of the body at one time, since some patients experience a skin reddening and a mild burning sensation that does not preclude treatment

DOSAGE AND ADMINSTRATION

HYDRO-Q® should be applied to the affected areas twice daily, morning and before bedtime or as directed by a physician.

During and after the use of HYDRO-Q®, sun exposure should be limited and a sunscreen agent or protective clothing should be used to cover up the treated areas to prevent regimentation. If no lightening effect is noted after two months of treatment, use of HYDRO-Q® should be discontinued. There is no recommended dosage for children under the age of 12 years of age except under the advice and supervision of a physician.

HOW SUPPLIED

HYDRO-Q® (Hydroquinone 4%) Gel is supplied in a 30 g tube.

NDC: 30815-0040-1

STORAGE AND HANDLING

Store at controlled room temperature, between 15° and 30°C (59°and 86°F).

REFERENCES

1. Denton C, Fitzpatrick TB, Lerner AB. Inhibition of melanin formation by chemical agents. J Invest Dermatology. 1952; 18: 119-135.
2. Fitzpatrick TB, Jimbow K, Obata M, Panthak M. Mechanism of depigmentation by hydroquinone. J Invest Dermatology. 1974; 62: 436-449.
3. Anderson RR, Parrish JA, Pitts D, Urbach F. UVA, Biological Effects of Ultraviolet Radiation With Emphasis on Human Responses to Longwave Ultraviolet. New York and London: Plenum Press; 1978: 151.

Distributed by:
DermAvance Pharmaceuticals, Malvern, PA 19355
NDC 30815-0040-1

P15132917-1

I2430214

PRINCIPAL DISPLAY PANEL - 30 g Tube Box

NDC 30815-0040-1

Rx Only

HYDRO-Q 4% GEL®

(Hydroquinone 4%) Gel®

SKIN BLEACHING GEL

DermAvance®
Advanced Skin Care
www.DermAvance.com

30 g